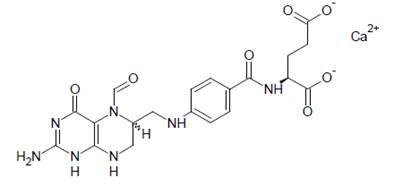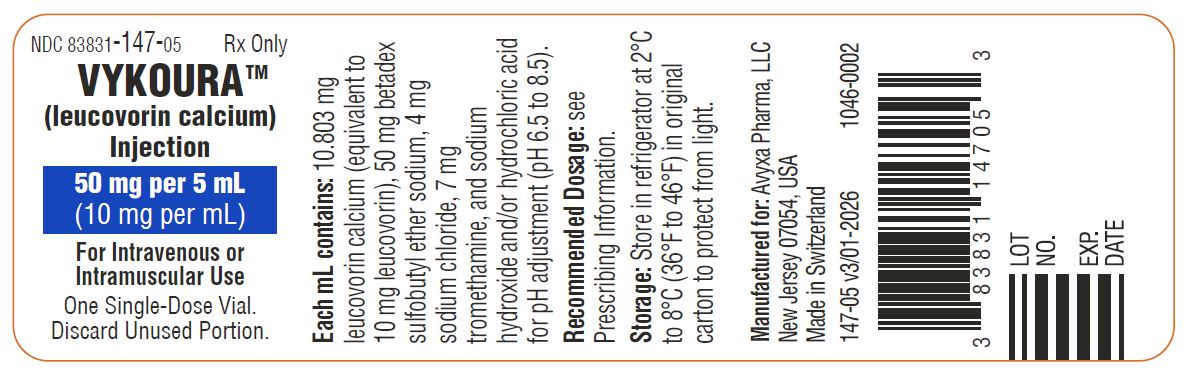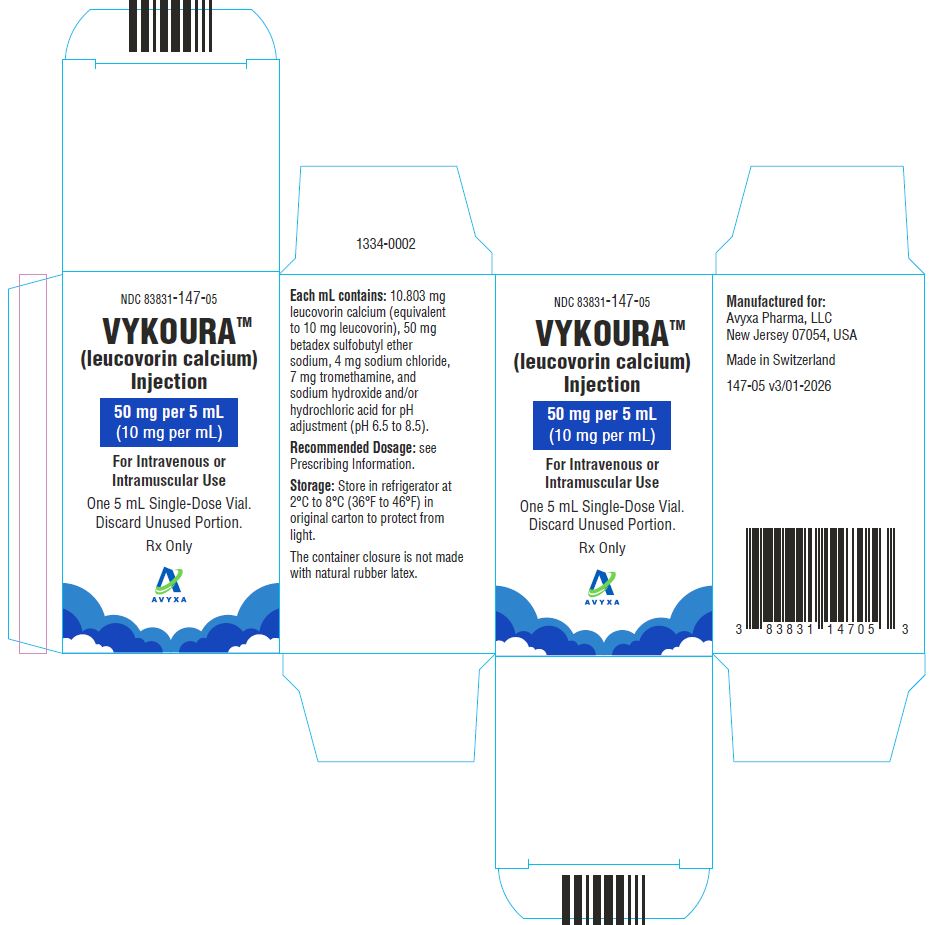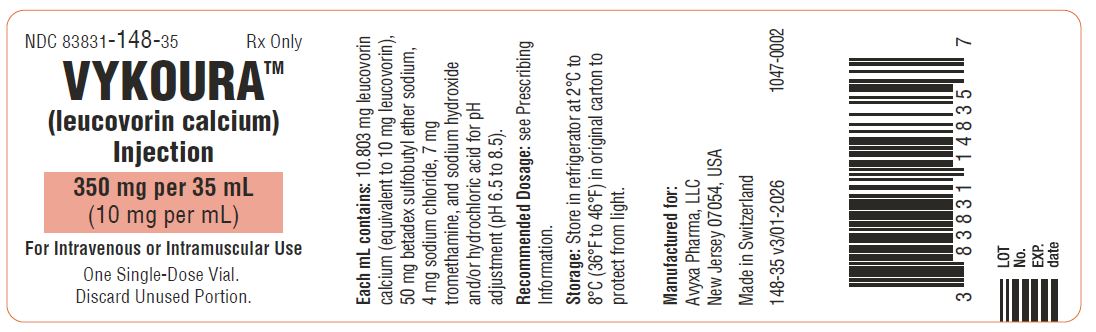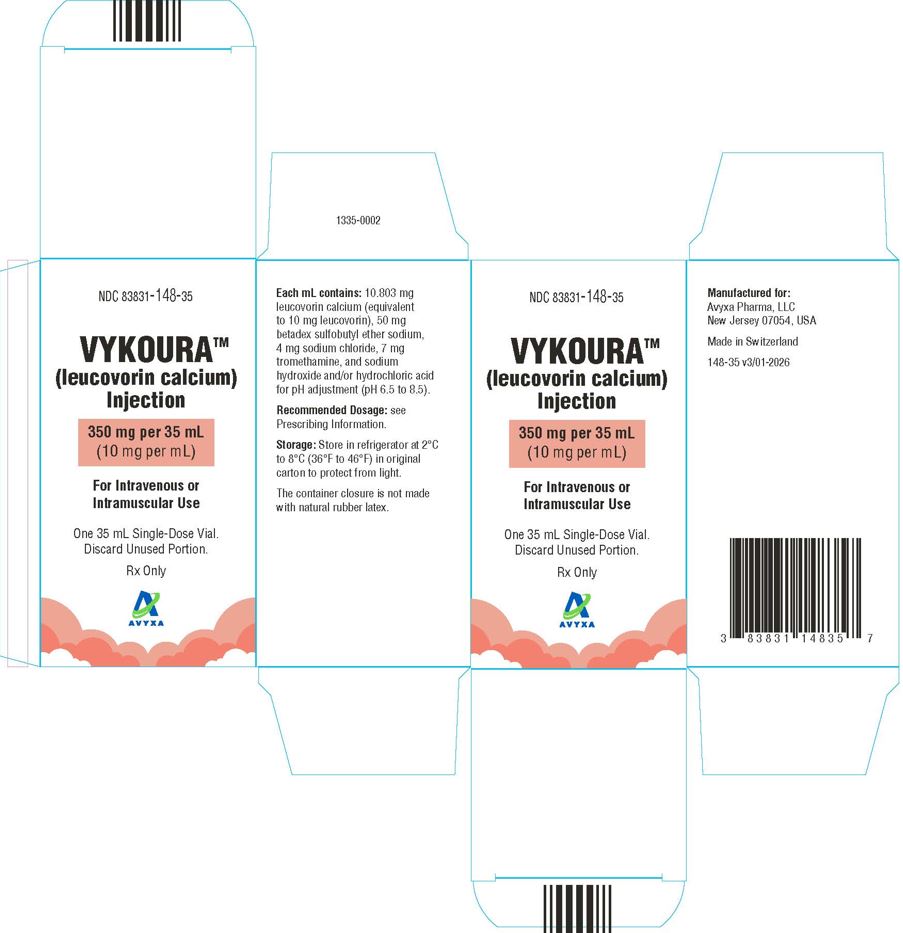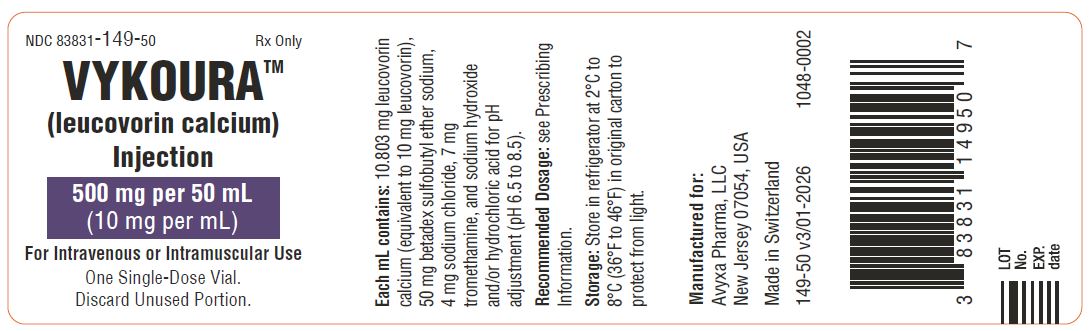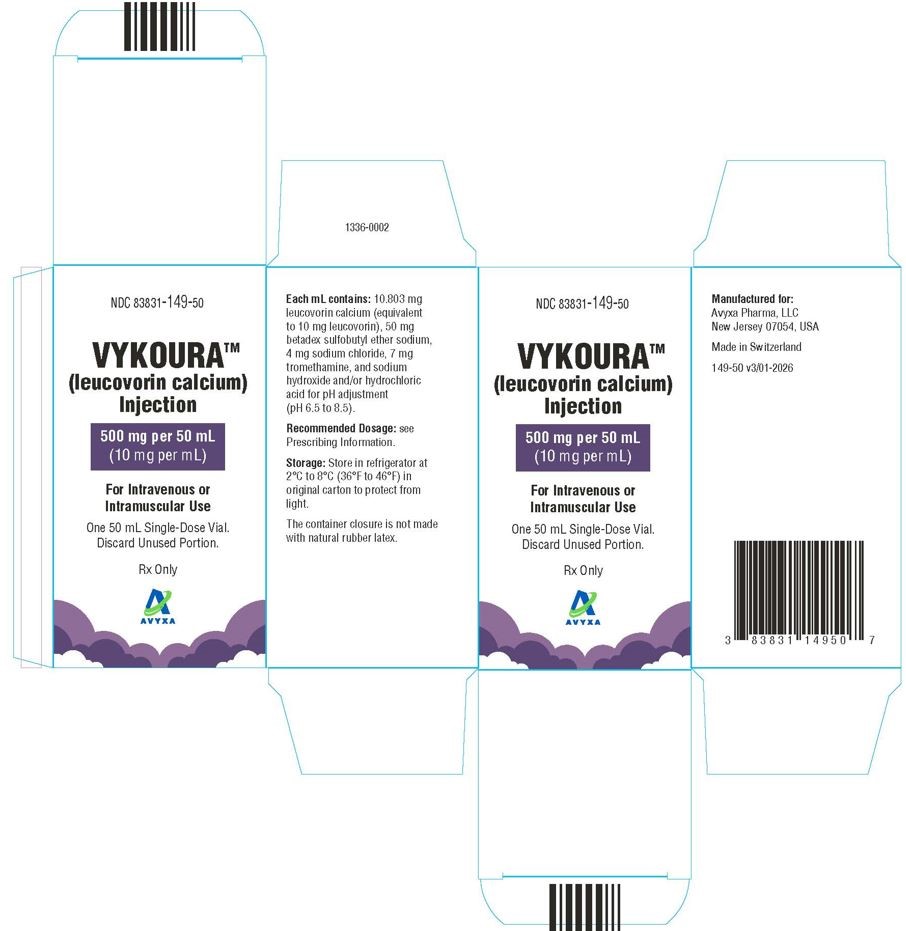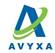 DRUG LABEL: VYKOURA
NDC: 83831-147 | Form: INJECTION
Manufacturer: Avyxa Pharma, LLC
Category: prescription | Type: HUMAN PRESCRIPTION DRUG LABEL
Date: 20260205

ACTIVE INGREDIENTS: LEUCOVORIN CALCIUM 50 mg/5 mL
INACTIVE INGREDIENTS: SODIUM CHLORIDE; TROMETHAMINE; BETADEX SULFOBUTYL ETHER SODIUM; SODIUM HYDROXIDE; HYDROCHLORIC ACID

HIGHLIGHTS OF PRESCRIBING INFORMATION

These highlights do not include all the information needed to use VYKOURA safely and effectively. See full prescribing information for VYKOURA.
VYKOURATM (leucovorin calcium) injection, for intravenous or intramuscular use
Initial U.S. Approval: 1952

1 INDICATIONS AND USAGE

VYKOURA is a folate analog indicated for:

- Rescue after high-dose methotrexate therapy in adult and pediatric patients. (1.1)
- Reducing the toxicity of
  - methotrexate in adult and pediatric patients with impaired methotrexate elimination or
  - folic acid antagonists or dihydrofolate reductase (DHFR) inhibitors following an overdose in adult and pediatric patients. (1.2)
- Treatment of megaloblastic anemias due to folic acid deficiency in adult and pediatric patients when oral therapy is not feasible. (1.3)
- Treatment of patients with metastatic colorectal cancer in combination with 5-fluorouracil. (1.4)

Limitations of Use:

VYKOURA is not indicated for the treatment of pernicious anemia and megaloblastic anemia secondary to lack of vitamin B12, because of the risk of progression of neurologic manifestations despite hematologic remission. (1.3)

2 DOSAGE AND ADMINISTRATION

VYKOURA is indicated for intravenous or intramuscular administration. Do not administer intrathecally. (2.1)

Rescue After High-Dose Methotrexate Therapy:

- Rescue recommendations are based on methotrexate dose of 12 to 15 grams/m^2administered by intravenous infusion over 4 hours. Initiate rescue at a dose of 15 mg (approximately 10 mg/m^2) every 6 hours beginning 24 hours after the beginning of methotrexate infusion. (2.2)
- Continue until the methotrexate level is below 0.05 micromolar (5 x 10^-8M). Adjust dose, if necessary, based on methotrexate elimination. (2.2)

Reducing the Toxicity of Methotrexate in Patients with Impaired Methotrexate Elimination or Following an Overdosage of Folic Acid Antagonists or DHFR Inhibitors:

- Start as soon as possible after methotrexate overdosage or within 24 hours of delayed methotrexate elimination. (2.3)
- Administer VYKOURA 10 mg/m^2intravenously or intramuscularly every 6 hours until methotrexate level is less than 0.01 micromolar (1 x 10^-8M). (2.3)

Metastatic Colorectal Cancer in Combination with Fluorouracil:

- 20 mg/m^2to 500 mg/m^2based on specific combination regimen.
- Administer VYKOURA before fluorouracil. (2.4)
- Do not mix VYKOURA with other drugs or administer other drugs through the same intravenous line. (2.4).

Megaloblastic Anemia Due to Folic Acid Deficiency:

- Up to 1 mg/day administered intravenously until adequate hematologic response is achieved.

3 DOSAGE FORMS AND STRENGTHS

Injection: 50 mg/5 mL, 350 mg/35 mL, and 500 mg/50 mL (10 mg/mL) in a single-dose vial. (3)

4 CONTRAINDICATIONS

VYKOURA is contraindicated in patients who have had a severe hypersensitivity reaction to leucovorin (folinic acid), levoleucovorin, or folic acid. (4)

5 WARNINGS AND PRECAUTIONS

- Hypersensitivity: Hypersensitivity reactions, including anaphylactic reactions and urticaria can occur. Withhold or permanently discontinue VYKOURA based on the severity of hypersensitivity. (5.1)
- Hypercalcemia: Due to calcium content, inject no more than 16 mL (160 mg) of VYKOURA intravenously per minute. (5.2)
- Risk of Administration Errors: Do not administer VYKOURA intrathecally. (5.3)

6 ADVERSE REACTIONS

- The most common adverse reactions (≥20%) in patients receiving high-dose methotrexate therapy with leucovorin rescue are stomatitis and vomiting. (6.1)
- The most common adverse reactions (>50%) in patients receiving leucovorin in combination with fluorouracil for metastatic colorectal cancer are stomatitis, diarrhea, and nausea. (6.1)

To report SUSPECTED ADVERSE REACTIONS, contact Avyxa Pharma, LLC at 1-888-520-0954 or FDA at 1-800-FDA-1088 or www.fda.gov/medwatch.

FULL PRESCRIBING INFORMATION

1 INDICATIONS AND USAGE

VYKOURA is indicated for:

1.1 Rescue after high-dose methotrexate (MTX) therapy in adult and pediatric patients.

1.2 Reducing the toxicity of:

- Methotrexate in adult and pediatric patients with impaired methotrexate elimination or
- Folic acid antagonists or dihydrofolate reductase (DHFR) inhibitors following an overdose in adult and pediatric patients.

1.3 Treatment of megaloblastic anemias due to folic acid deficiency in adult and pediatric patients when oral therapy is not feasible.

1.4 Treatment of patients with metastatic colorectal cancer in combination with fluorouracil.

Limitations of Use

VYKOURA is not indicated for pernicious anemia and megaloblastic anemia secondary to the lack of vitamin B12, because of the risk of progression of neurologic manifestations despite hematologic remission.

2 DOSAGE AND ADMINISTRATION

2.1 Important Administration Information

- VYKOURA is indicated for intravenous (IV) and intramuscular (IM) administration. Do not administer intrathecally. VYKOURA may be harmful or fatal if given intrathecally.
- Do NOT mix VYKOURA with other drugs or administer other drugs through the same intravenous line. A precipitate may form if VYKOURA is mixed with fluorouracil.
- Due to the calcium content of VYKOURA, do NOT exceed the maximum infusion rate of 160 mg/minute to avoid hypercalcemia. [See Warnings and Precautions (5.2)]

2.2 Recommended Dosage for Rescue After High-Dose Methotrexate Therapy

- The recommended dosage for VYKOURA is based on serum methotrexate levels obtained 24 hours following the methotrexate infusion (refer to the methotrexate prescribing information). Table 1 describes the VYKOURA regimen in patients who receive a dose of 12-15 grams/m^2of methotrexate. Consult institutional guidelines for additional dosing information as appropriate.
- Begin VYKOURA twenty-four hours after starting the methotrexate infusion. As the time interval between methotrexate administration and VYKOURA increases, the effectiveness of VYKOURA to diminish methotrexate toxicity may decrease.
- VYKOURA may be administered intravenously or intramuscularly [see Dosage and Administration (2.6)].
- Monitor serum creatinine and methotrexate levels at least once daily. Administer intravenous fluids (3 Liters per day) and alkalinize the urine to a pH of 7 or greater until the methotrexate level is below 0.05 micromolar (5 x 10^-8M).

Table 1 Recommended Dosage for VYKOURA After High-Dose Methotrexate Based on Serum Methotrexate and Serum Creatinine Levels
Clinical Situation | Laboratory Findings | Recommended Dosage
Normal Methotrexate Elimination | Serum methotrexate level approximately 10 micromolar at 24 hours after administration, 1 micromolar at 48 hours, and less than 0.2 micromolar at 72 hours. | 15 mg intravenously or intramuscularly every 6 hours for 60 hours for a total of 10 doses. Begin VYKOURA 24 hours after the start of methotrexate infusion.
Delayed Late Methotrexate Elimination | Serum methotrexate level remaining above 0.2 micromolar at 72 hours, and more than 0.05 micromolar at 96 hours after administration. | Continue 15 mg intravenously or intramuscularly every 6 hours, until methotrexate level is less than 0.05 micromolar.
Delayed Early Methotrexate Elimination and/or Evidence of Acute Renal Injury* | Serum methotrexate level of 50 micromolar or more at 24 hours, or 5 micromolar or more at 48 hours after administration, OR 100% or greater increase in serum creatinine level at 24 hours after methotrexate administration (e.g., an increase from 0.5 mg/dL to a level of 1 mg/dL or more). | 150 mg intravenously or intramuscularly every 3 hours, until methotrexate level is less than 1 micromolar; then 15 mg intravenously or intramuscularly every 3 hours until methotrexate level is less than 0.05 micromolar.
* These patients are likely to develop reversible renal failure. In addition to appropriate VYKOURA therapy, continue hydration and urinary alkalinization and monitor fluid and electrolyte status, until the serum methotrexate level has fallen to below 0.05 micromolar and the renal failure has resolved.

Extend VYKOURA rescue for an additional 24 hours (total of 14 doses over 84 hours) in subsequent courses of methotrexate in patients with:

- Impaired methotrexate elimination including third-space fluid accumulation and inadequate hydration
- Renal impairment

2.3 Recommended Dosage to Reduce Toxicity of Folic Acid Antagonists or Dihydrofolate Reductase (DHFR) Inhibitors or for Impaired Methotrexate Elimination

Start VYKOURA as soon as possible after an inadvertent overdosage of methotrexate or within 24 hours of methotrexate administration when methotrexate elimination is impaired. As the time interval between methotrexate administration and VYKOURA increases, the effectiveness of VYKOURA to diminish methotrexate toxicity may decrease.

Administer VYKOURA 10 mg/m^2 intravenously or intramuscularly every 6 hours until the serum methotrexate level is less than 0.01 micromolar (1 x 10^-8 M).

Monitor serum creatinine and methotrexate levels at least every 24 hours. Increase the dosage of VYKOURA to 100 mg/m^2 intravenously every 3 hours if

- serum creatinine at 24-hours increases 50% or more compared to baseline
- the methotrexate level at 24-hours is greater than 5 micromolar (5 x 10^-6M)
- the methotrexate level at 48-hours is greater than 0.9 micromolar (9 x 10^-7M)

Continue VYKOURA at the same dosage until the methotrexate level is less than 0.01 micromolar (1 x 10^-8 M).

Continue intravenous fluids (3 L per day) and sodium bicarbonate. Adjust the sodium bicarbonate dose to maintain urine pH at 7.0 or greater.

2.4 Recommended Dosage in Combination with Fluorouracil for Advanced Colorectal Cancer

Administer VYKOURA intravenously prior to fluorouracil.

Dosage of VYKOURA in combination with fluorouracil varies by regimen and ranges from 20 mg/m^2 to 500 mg/m^2. Consult institutional guidelines for recommended dosing, dosing frequency, and duration of therapy.

Refer to the Prescribing Information for fluorouracil and other drugs used in combination with VYKOURA for additional information on management of adverse reactions.

2.5 Recommended Dosage for Megaloblastic Anemia Due to Folic Acid Deficiency

Up to 1 mg daily administered intravenously until adequate hematologic response is achieved. There is no evidence that doses greater than 1 mg/day have greater efficacy than those of 1 mg; additionally, loss of folate in urine becomes roughly logarithmic as the amount administered exceeds 1 mg.

2.6 Preparation and Administration

Parenteral drug products should be inspected visually for particulate matter and discoloration prior to administration, whenever solution and container permit.

For Intravenous Injection

Preparation

- Select the appropriate number of vial(s) based on the prescribed dose.
- Withdraw the calculated dose into a sterile syringe and administer immediately.
- Discard partially used or empty vials as VYKOURA does not contain any preservatives.

Administration

- Administer VYKOURA slowly. Do not exceed an intravenous administration rate of 160 mg per minute (16 mL per minute) to avoid hypercalcemia[see Warnings and Precautions (5.2)].

For Intramuscular Injection

Preparation

- Select the appropriate number of vial(s) based on the prescribed dose.
- Withdraw the calculated dose into a sterile syringe and administer immediately.
- Discard partially used or empty vials as VYKOURA does not contain any preservatives.

Administration

- Administer the prescribed dose of VYKOURA by intramuscular injection using standard aseptic technique.

3 DOSAGE FORMS AND STRENGTHS

Injection: 50 mg/5 mL (10 mg/mL), 350 mg/35 mL (10 mg/mL), and 500 mg/50 mL (10 mg/mL) of leucovorin as a clear, colorless to yellow color solution in a single-dose vial.

4 CONTRAINDICATIONS

VYKOURA is contraindicated in patients who have had a severe hypersensitivity reaction to leucovorin (folinic acid), levoleucovorin, or folic acid [see Warnings and Precautions (5.1)]. Reactions have included anaphylactic reactions.

5 WARNINGS AND PRECAUTIONS

5.1 Hypersensitivity

Hypersensitivity reactions, including anaphylactic reactions and urticaria, have been reported following the administration of leucovorin. VYKOURA is contraindicated in patients who have had a severe hypersensitivity reaction to leucovorin, levoleucovorin, or folic acid [see Contraindications (4)]. Withhold or permanently discontinue VYKOURA based on the severity of hypersensitivity.

5.2 Hypercalcemia

Because of the calcium content of the VYKOURA, do not administer more than 160 mg of VYKOURA intravenously per minute [see Dosing and Administration (2.6)].

5.3 Risk of Administration Errors

In the treatment of accidental overdosages of intrathecally administered folic acid antagonists, do not administer VYKOURA intrathecally. VYKOURA MAY BE HARMFUL OR FATAL IF GIVEN INTRATHECALLY.

6 ADVERSE REACTIONS

The following clinically significant adverse reactions are described elsewhere in the labeling:

- Hypersensitivity [see Warnings and Precautions (5.1)]
- Hypercalcemia [see Warnings and Precautions (5.2)]

6.1 Clinical Trials Experience

Because clinical trials are conducted under widely varying conditions, adverse reaction rates observed in the clinical trials of a drug cannot be directly compared to rates in the clinical trials of another drug and may not reflect the rates observed in clinical practice.

Table 2 summarizes significant adverse events occurring in 316 patients treated with the leucovorin/5-fluorouracil combinations compared against 70 patients treated with 5-fluorouracil alone for advanced colorectal carcinoma. These data are taken from the Mayo/NCCTG large multicenter prospective trial evaluating the efficacy and safety of the combination regimen.

Table 2: Percentage of Patients Treated with Leucovorin and Fluorouracil for Advanced Colorectal Carcinoma Reporting Adverse Experiences or Hospitalized for Toxicity
 | (High LV)/5-FU (N = 155) |  | (Low LV)/5-FU (N = 161) |  | 5-FU Alone (N = 70)
 | Any (%) | Grade 3+ (%) | Any (%) | Grade 3+ (%) | Any (%) | Grade 3+ (%)
Leukopenia | 69 | 14 | 83 | 23 | 93 | 48
Thrombocytopenia | 8 | 2 | 8 | 1 | 18 | 3
Infection | 8 | 1 | 3 | 1 | 7 | 2
Nausea | 74 | 10 | 80 | 9 | 60 | 6
Vomiting | 46 | 8 | 44 | 9 | 40 | 7
Diarrhea | 66 | 18 | 67 | 14 | 43 | 11
Stomatitis | 75 | 27 | 84 | 29 | 59 | 16
Constipation | 3 | 0 | 4 | 0 | 1 | -
Lethargy/Malaise/Fatigue | 13 | 3 | 12 | 2 | 6 | 3
Alopecia | 42 | 5 | 43 | 6 | 37 | 7
Dermatitis | 21 | 2 | 25 | 1 | 13 | -
Anorexia | 14 | 1 | 22 | 4 | 14 | -
Hospitalization for Toxicity | 5% |  | 15% |  | 7%
High LV = Leucovorin 200 mg/m^2, Low LV = Leucovorin 20 mg/m^2
Any = percentage of patients reporting toxicity of any severity
Grade 3+ = percentage of patients reporting toxicity of Grade 3 or higher

7 DRUG INTERACTIONS

7.1 Effects of Other Drugs on VYKOURA

Glucarpidase

Administer VYKOURA at least 2 hours before or 2 hours after the glucarpidase dose when administering concomitantly.

Glucarpidase can decrease leucovorin concentrations, which may decrease the effect of leucovorin rescue.

7.2 Effects of VYKOURA on Other Drugs

Certain Antiepileptic Drugs

Increase monitoring for seizure activity in patients taking certain concomitant antiepileptic drugs.

Folic acid in high doses may reduce the effectiveness of certain antiepileptic drugs (e.g., phenobarbital, phenytoin, and primidone) and thereby increase the frequency of seizures. It is not known whether folinic acid, including VYKOURA, has the same effects; however, both folic and folinic acids, including VYKOURA share some common metabolic pathways.

Trimethoprim-Sulfamethoxazole

Avoid concomitant use of VYKOURA with trimethoprim-sulfamethoxazole. The effectiveness of trimethoprim-sulfamethoxazole can be decreased if used concomitantly with VYKOURA which was associated with increased rates of treatment failure and mortality in patients with HIV infection who receive trimethoprim-sulfamethoxazole for the acute treatment of Pneumocystis jirovecii pneumonia.

8 USE IN SPECIFIC POPULATIONS

8.1 Pregnancy

Risk Summary

Available data on the use of leucovorin during pregnancy have not identified a drug-associated risk of major birth defects, miscarriage, or adverse maternal or fetal outcomes.

Adequate animal reproduction studies have not been conducted with leucovorin.

Agents administered in combination with VYKOURA may cause fetal harm. Refer to the Prescribing Information for agents administered in combination with VYKOURA for additional information, as appropriate.

In the U.S. general population, the estimated background risk of major birth defects and miscarriage in clinically recognized pregnancies is 2% to 4% and 15% to 20%, respectively.

8.2 Lactation

Risk Summary

There are no available data on the presence of leucovorin in either human or animal milk, the effect on the breastfed infant, or on milk production. The developmental and health benefits of breastfeeding should be considered along with the mother's clinical need for VYKOURA and any potential adverse effects on the breastfed infant from VYKOURA or from the underlying maternal condition.

Refer to the Prescribing Information for agents administered in combination with VYKOURA for breastfeeding recommendations, as appropriate.

8.4 Pediatric Use

VYKOURA is indicated to reduce the toxicity of MTX in pediatric patients with impaired MTX elimination, and folic acid antagonists or dihydrofolate reductase (DHFR) inhibitors following an overdose.

8.5 Geriatric Use

Clinical studies of leucovorin calcium did not show differences in safety or effectiveness between subjects over 65 and younger subjects. Other clinical experience has not identified differences in responses between the elderly and younger patients, but greater sensitivity of some older patients cannot be ruled out. This drug is known to be excreted by the kidney and the risk of toxic reactions to the drug may be greater in patients with impaired renal function. Because elderly patients are more likely to have decreased renal function, care should be taken in dose selection in this patient population.

11 DESCRIPTION

Leucovorin is a folate analog, also known as folinic acid, Citrovorum factor, or 5-formyl-5,6,7,8-tetrahydrofolic acid calcium salt. This compound has the chemical designation of Calcium N-(p-((((6RS)-2-amino-5-formyl 5,6,7,8-tetrahydro-4-hydroxy-6-pteridinyl)methyl)amino)benzoyl)-L-glutamate (1:1). The structural formula of leucovorin calcium is:

Leucovorin calcium is a white to light yellow crystalline powder with the molecular formula C20H21N7O7Ca and a molecular weight of 511.50 (calculated on the anhydrous basis).

VYKOURA (leucovorin calcium), for intravenous and intramuscular use, is supplied as a sterile, preservative-free, clear, colorless to yellow solution available in 50 mg/5 mL, 350 mg/35 mL and 500 mg/50 mL single-dose vials containing 10 mg/mL of leucovorin. Each mL contains 10.803 mg leucovorin calcium (equivalent to 10 mg leucovorin), 50 mg betadex sulfobutyl ether sodium, 4 mg sodium chloride, 7 mg tromethamine, and sodium hydroxide and/or hydrochloric acid for pH adjustment (pH 6.5 to 8.5).

There is 0.004 mEq of calcium per mg of leucovorin.

12 CLINICAL PHARMACOLOGY

12.1 Mechanism of Action

High-Dose Methotrexate Therapy

Leucovorin is a mixture of the diastereoisomers of the 5-formyl derivative of tetrahydrofolic acid (THF). The biologically active compound of the mixture is the (-)-l isomer, known as Citrovorum factor or (-)-folinic acid. Leucovorin does not require reduction by the enzyme dihydrofolate reductase in order to participate in reactions utilizing folates as a source of "one-carbon" moieties. l-Leucovorin (l-5 formyltetrahydrofolate) is rapidly metabolized (via 5, 10-methenyltetrahydrofolate then 5, 10-methylenetetrahydrofolate) to l-5-methyltetrahydrofolate. L-5-methyltetrahydrofolate can in turn be metabolized via other pathways back to 5,10 methylenetetrahydrofolate, which is converted to 5-methyltetrahydrofolate by an irreversible, enzyme catalyzed reduction using the cofactors FADH2 and NADPH. Administration of leucovorin can counteract the therapeutic and toxic effects of folic acid antagonists such as methotrexate, which act by inhibiting dihydrofolate reductase.

Combination with Fluorouracil in Colorectal Cancer

Leucovorin can enhance the therapeutic and toxic effects of fluoropyrimidines used in cancer therapy, such as 5-fluorouracil. Concurrent administration of leucovorin does not appear to alter the plasma pharmacokinetics of 5-fluorouracil. 5-Fluorouracil is metabolized to fluorodeoxyuridylic acid, which binds to and inhibits the enzyme thymidylate synthase (an enzyme important in DNA repair and replication). Leucovorin is readily converted to another reduced folate, 5,10-methylenetetrahydrofolate, which acts to stabilize the binding of fluorodeoxyuridylic acid to thymidylate synthase and thereby enhances the inhibition of this enzyme.

12.2 Pharmacodynamics

Leucovorin exposure-response relationships and time course of pharmacodynamic response is not fully characterized.

12.3 Pharmacokinetics

Leucovorin pharmacokinetics were observed after a single intramuscular dose of 10 mg/m^2 in healthy subjects and are presented as mean (CV%) unless otherwise specified. Leucovorin baseline-corrected maximum plasma concentration (Cmax) is 1,832 ng/mL (14%) and the total systemic exposure (AUC) is 23,043 ng*hr/mL (15%).

Absorption

Leucovorin median (min, max) time to maximum plasma concentration (Tmax) is 1.7 hours (0.7, 4.5).

Elimination

Leucovorin estimated terminal half-life is approximately 9.5 hours (CV 17%).

Metabolism

Leucovorin is rapidly metabolized (via 5, 10-methenyltetrahydrofolate then 5, 10-methylenetetrahydrofolate) to l,5-methyltetrahydrofolate. l,5-Methyltetrahydrofolate can be metabolized via other pathways back to 5,10-methylenetetrahydrofolate, which is converted to 5-methyltetrahydrofolate by an irreversible, enzyme catalyzed reduction using the cofactors FADH2 and NADPH.

13 NONCLINICAL TOXICOLOGY

13.1 Carcinogenesis, Mutagenesis, Impairment of Fertility

No studies have been conducted to evaluate the potential of leucovorin for carcinogenesis, mutagenesis and impairment of fertility.

16 HOW SUPPLIED/STORAGE AND HANDLING

VYKOURA (leucovorin calcium) injection is a clear, colorless to yellow color solution supplied in single-dose vial. Each carton contains one single-dose vial delivering 10 mg/mL leucovorin in the following strengths:

Strength | NDC Number
50 mg/5 mL (10 mg/mL) | 83831-147-05
350 mg/35 mL (10 mg/mL) | 83831-148-35
500 mg/50 mL (10 mg/mL) | 83831-149-50

This container closure is not made with natural rubber latex.

Storage and Handling

Store in refrigerator at 2°C to 8°C (36°F to 46°F) in original carton to protect from light.

17 PATIENT COUNSELING INFORMATION

Advise patients of the following risks of VYKOURA:

Hypersensitivity Reactions

Inform patients that hypersensitivity reactions can occur with VYKOURA including anaphylactic reactions and urticaria. Inform patients about the signs and symptoms of hypersensitivity reactions and to contact their healthcare provider immediately if these occur during or after the administration of VYKOURA [see Warnings and Precautions (5.1)].

Hypercalcemia

Advise patients that hypercalcemia may occur with the use of VYKOURA and to report nausea, vomiting, headache and decreased alertness during or after the administration of VYKOURA. [see Warnings and Precautions (5.2)].

Drug Interactions

Advise patients to inform their health care providers of all concomitant drugs, including prescription drugs, nonprescription drugs, vitamins, and herbal products [see Drug Interactions (7)].

Manufactured for:

Avyxa Pharma, LLC

New Jersey 07054, USA

Made in Switzerland

PACKAGE LABEL.PRINCIPAL DISPLAY PANEL

VYKOURA (leucovorin) Injection, 50 mg/5 mL -Container Label
VYKOURA (leucovorin) Injection, 50 mg/5 mL -Carton Label
VYKOURA (leucovorin) Injection, 350 mg/35 mL -Container Label
VYKOURA (leucovorin) Injection, 350 mg/35 mL -Carton Label
VYKOURA (leucovorin) Injection, 500 mg/50 mL -Conatiner Label
VYKOURA (leucovorin) Injection, 500 mg/50 mL -Carton Label